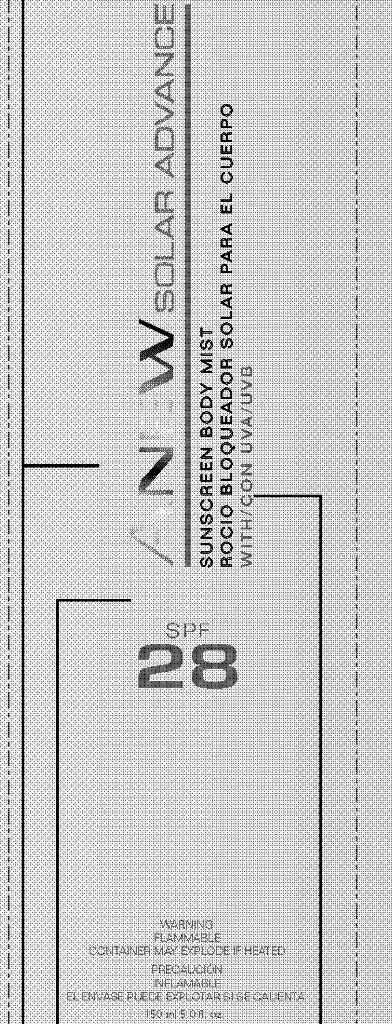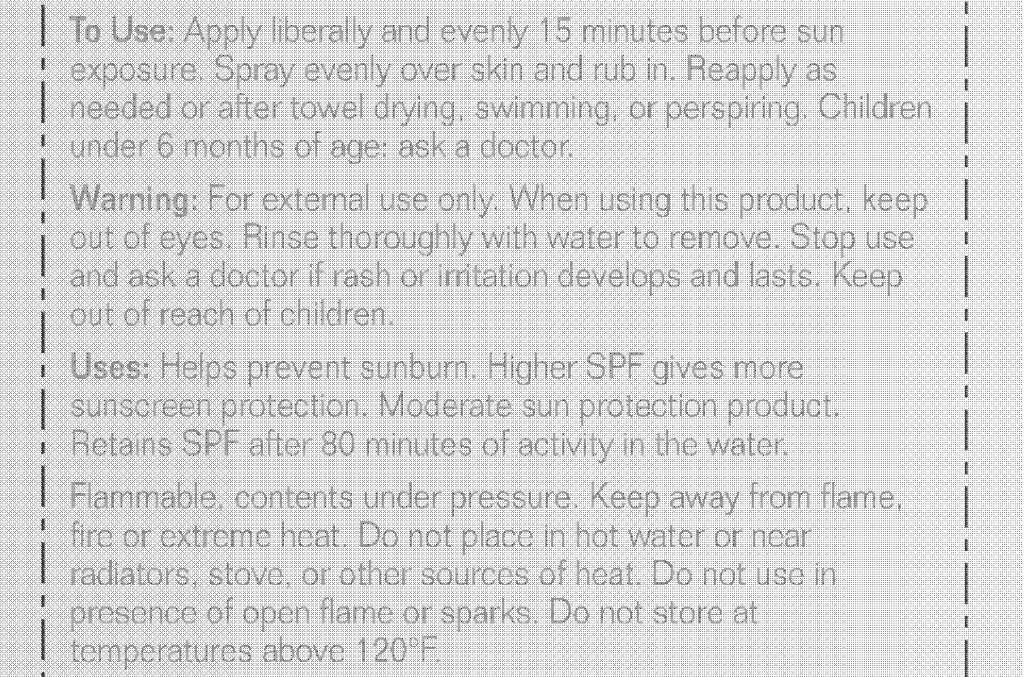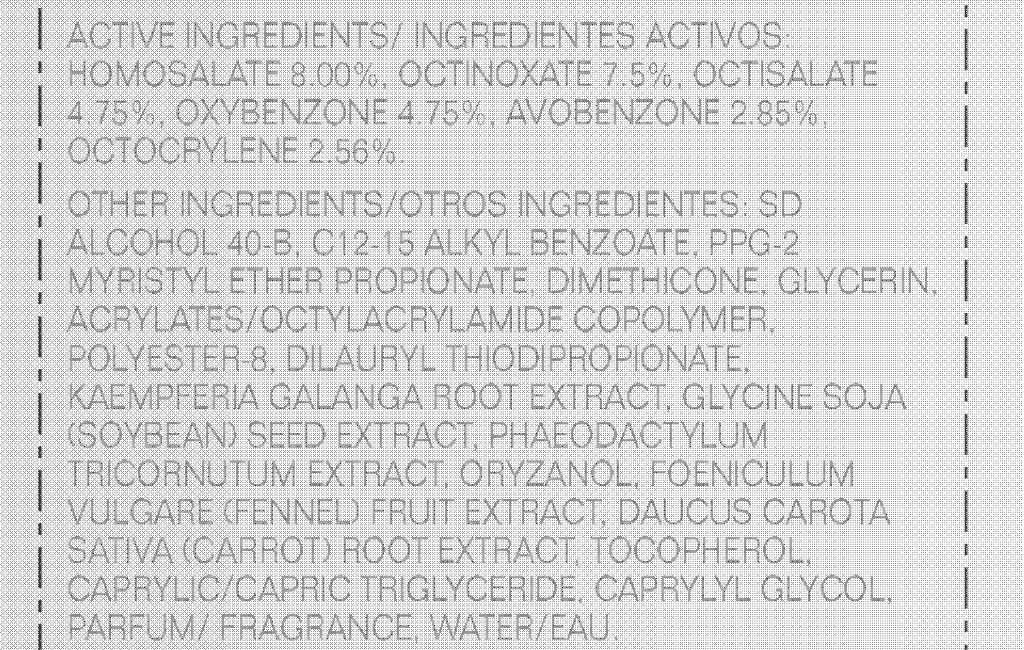 DRUG LABEL: ANEW Solar Advance
NDC: 10096-0254 | Form: SPRAY
Manufacturer: Avon Products, Inc.
Category: otc | Type: HUMAN OTC DRUG LABEL
Date: 20110411

ACTIVE INGREDIENTS: HOMOSALATE	 12 mL/150 mL; OCTINOXATE	 11.25 mL/150 mL; OCTISALATE	 7.125 mL/150 mL; OXYBENZONE	 7.125 mL/150 mL; AVOBENZONE	 4.275 mL/150 mL; OCTOCRYLENE	 3.84 mL/150 mL

DOSAGE AND ADMINISTRATION

To Use: Apply liberally and evenly 15 minutes before sun
exposure. Spray evenly over skin and rub in. Reapply as
needed or after towel drying, swimming, or perspiring. Children
under 6 months of age: ask a doctor.

WARNINGS

Warning: For external use only. When using this product, keep
out of eyes. Rinse thoroughly with water to remove. Stop use
and ask a doctor if rash or irritation develops and lasts. Keep
out of reach of children.

INDICATIONS AND USAGE

Uses: Helps prevent sunburn. Higher SPF gives more
sunscreen protection. Moderate sun protection product.
Retains SPF after 80 minutes of activity in the water.

SAFE HANDLING WARNING

Flammable, contents under pressure. Keep away from flame,
fire or extreme heat. Do not place in hot water or near
radiators, stove, or other sources of heat. Do not use in
presence of open flame or sparks. Do not store at
temperatures above 120°F.

ACTIVE INGREDIENTS/ INGREDIENTES ACTIVOS:
HOMOSALATE 8.00%, OCTINOXATE 7.5%, OCTISALATE
4.75%, OXYBENZONE 4.75%, AVOBENZONE 2.85%,
OCTOCRYLENE 2.56%.

INACTIVE INGREDIENT

OTHER INGREDIENTS/OTROS INGREDIENTES: SD
ALCOHOL 40-B, C12-15 ALKYL BENZOATE, PPG-2
MYRISTYL ETHER PROPIONATE, DIMETHICONE, GLYCERIN,
ACRYLATES/OCTYLACRYLAMIDE COPOLYMER,
POLYESTER-8, DILAURYL THIODIPROPIONATE,
KAEMPFERIA GALANGA ROOT EXTRACT, GLYCINE SOJA
(SOYBEAN) SEED EXTRACT, PHAEODACTYLUM
TRICORNUTUM EXTRACT, ORYZANOL, FOENICULUM
VULGARE (FENNEL) FRUIT EXTRACT, DAUCUS CAROTA
SATIVA (CARROT) ROOT EXTRACT, TOCOPHEROL,
CAPRYLIC/CAPRIC TRIGLYCERIDE, CAPRYLYL GLYCOL,
PARFUM/ FRAGRANCE, WATER/EAU.